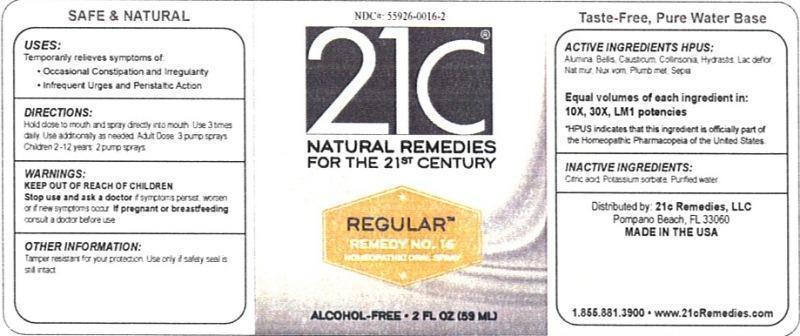 DRUG LABEL: Regular Remedies No. 16
NDC: 55926-0016 | Form: LIQUID
Manufacturer: Speer Laboratories, LLC
Category: homeopathic | Type: HUMAN OTC DRUG LABEL
Date: 20130730

ACTIVE INGREDIENTS: ALUMINUM OXIDE 10 [hp_X]/59 mL; BELLIS PERENNIS 10 [hp_X]/59 mL; CAUSTICUM 10 [hp_X]/59 mL; COLLINSONIA CANADENSIS ROOT 10 [hp_X]/59 mL; GOLDENSEAL 10 [hp_X]/59 mL; SKIM MILK 10 [hp_X]/59 mL; SODIUM CHLORIDE 10 [hp_X]/59 mL; STRYCHNOS NUX-VOMICA SEED 10 [hp_X]/59 mL; LEAD 10 [hp_X]/59 mL; SEPIA OFFICINALIS JUICE 10 [hp_X]/59 mL
INACTIVE INGREDIENTS: CITRIC ACID MONOHYDRATE; POTASSIUM SORBATE; WATER

Regular Remedy No. 16

Active Ingredient HPUS: Alumina, Bellis perennis, Causticum, Collinsonia canadensis, Hydrastis canadensis, Lac defloratum, Natrum muriaticum, Nux vomica, Plumbum metallicum, Sepia. Equal volumes of each ingredient in: 10X, 30X, LM1 potencies

HPUS indicates that this ingredient is officially part of the Homeopathic Pharmacopia of the United States.

Inactive Ingredients: Citric acid, Potassium sorbate, Purified water.

INDICATIONS AND USAGE

Uses: Temporarily relieves symptoms of:

- Occasional constipation and irregularity
- Infrequent urges and peristaltic action

DOSAGE AND ADMINISTRATION

Directions: Hold close to mouth and spray directly into mouth. Use 3 times daily. Use additionally as needed. Adult Dose: 3 pump sprays. Children 2-12 years: 2 pump sprays.

Keep out of reach of children.

Warnings:

Stop use and ask a doctor if symptoms persist, worsen or if new symptoms occur. If pregnant or breastfeeding, consult a doctor before use.

Other Information: Tamper resistant for your protection. Use only if safety seal is still intact.

PURPOSE

Uses: Temporarily relieves symptoms of: occasional constipation and irregularity, infrequent urges and peristaltic action